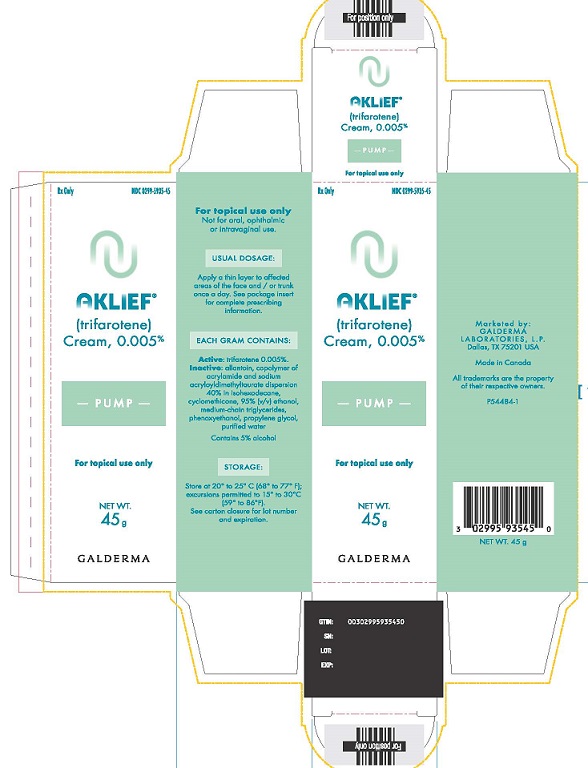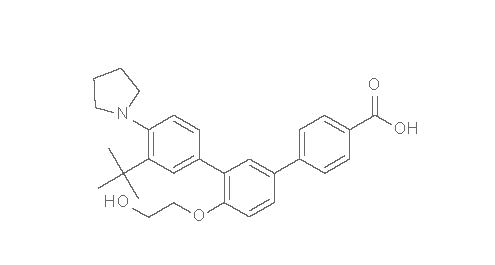 DRUG LABEL: AKLIEF
NDC: 0299-5935 | Form: CREAM
Manufacturer: Galderma Laboratories, L.P.
Category: prescription | Type: HUMAN PRESCRIPTION DRUG LABEL
Date: 20240916

ACTIVE INGREDIENTS: TRIFAROTENE 50 ug/1 g
INACTIVE INGREDIENTS: ALLANTOIN; ACRYLIC ACID/SODIUM ACRYLATE COPOLYMER (1:1; 600 MPA.S AT 0.2%); ISOHEXADECANE; CYCLOMETHICONE 5; ALCOHOL; MEDIUM-CHAIN TRIGLYCERIDES; PHENOXYETHANOL; PROPYLENE GLYCOL; WATER

HIGHLIGHTS OF PRESCRIBING INFORMATION

These highlights do not include all the information needed to use AKLIEF ®Cream safely and effectively. See full prescribing information for AKLIEF Cream.
AKLIEF(trifarotene) cream, for topical use
Initial U.S. Approval: 2019

1 INDICATIONS AND USAGE

AKLIEF Cream is a retinoid indicated for the topical treatment of acne vulgaris in patients 9 years of age and older. (1)

2 DOSAGE AND ADMINISTRATION

- For topical use only. Not for oral, ophthalmic or intravaginal use.
- Apply a thin layer of AKLIEF Cream to the affected areas of the face and/or trunk once a day, in the evening, on clean and dry skin. Avoid contact with the eyes, lips, paranasal creases, and mucous membranes. (2)

3 DOSAGE FORMS AND STRENGTHS

Cream: 0.005% trifarotene. (3)

4 CONTRAINDICATIONS

None (4)

5 WARNINGS AND PRECAUTIONS

- Skin irritation: Erythema, scaling, dryness, and stinging/burning may be experienced with use of AKLIEF Cream. Use a moisturizer from the initiation of treatment, and, if appropriate, reduce the frequency of application of AKLIEF Cream, suspend or discontinue use. (5.1)
- Ultraviolet Light and Environmental Exposure: Minimize exposure to sunlight and sunlamps. Use sunscreen and protective clothing over treated areas when exposure cannot be avoided. (5.2)

6 ADVERSE REACTIONS

Most common adverse reactions (incidence ≥ 1%) in patients treated with AKLIEF Cream were application site irritation, application site pruritus, and sunburn (6).

To report SUSPECTED ADVERSE REACTIONS, contact Galderma Laboratories, L.P. at 1-866-735-4137 or FDA at
1-800-FDA-1088 or www.fda.gov/medwatch.

FULL PRESCRIBING INFORMATION

1 INDICATIONS AND USAGE

AKLIEF Cream is a retinoid indicated for the topical treatment of acne vulgaris in patients 9 years of age and older.

2 DOSAGE AND ADMINISTRATION

Apply a thin layer of AKLIEF Cream to the affected areas once daily, in the evening, on clean and dry skin.

- One pump actuation should be enough to cover the face (i.e., forehead, cheeks, nose, and chin).
- Two actuations of the pump should be enough to cover the upper trunk (i.e., reachable upper back, shoulders and chest). One additional pump actuation may be used for middle and lower back if acne is present.

The use of a moisturizer is recommended as frequently as needed from the initiation of treatment.
Avoid contact with the eyes, lips, paranasal creases, mucous membranes.
AKLIEF Cream is for topical use only. Not for oral, ophthalmic, or intravaginal use.

3 DOSAGE FORMS AND STRENGTHS

Cream: 0.005%. Each gram of AKLIEF Cream contains 50 mcg of trifarotene in a white cream.

4 CONTRAINDICATIONS

None

5 WARNINGS AND PRECAUTIONS

5.1 Skin Irritation

Patients using AKLIEF Cream may experience erythema, scaling, dryness, and stinging/burning. Maximum severity of these reactions typically occurred within the first 4 weeks of treatment, and severity decreased with continued use of the medication. Depending upon the severity of these adverse reactions, instruct patients to use a moisturizer, reduce the frequency of application of AKLIEF Cream, or suspend use temporarily. If severe reactions persist the treatment may be discontinued.
Avoid application of AKLIEF Cream to cuts, abrasions, or eczematous or sunburned skin. Use of “waxing” as a depilatory method should be avoided on skin treated with AKLIEF Cream.

5.2 Ultraviolet Light and Environmental Exposure

Minimize unprotected exposure to ultraviolet rays (including sunlight and sunlamps) during treatment with AKLIEF Cream. Warn patients who normally experience high levels of sun exposure and those with inherent sensitivity to sun to exercise caution. Use of sunscreen products and protective clothing over treated areas is recommended when exposure cannot be avoided.

6 ADVERSE REACTIONS

6.1 Clinical trials experience

Because clinical trials are conducted under widely varying conditions, adverse reaction rates observed in the clinical trials of a drug cannot be directly compared with rates in the clinical trials of another drug and may not reflect rates observed in practice. In the three Phase 3 clinical trials, 1673 subjects with acne vulgaris on the face and trunk, 9 years and older were exposed to AKLIEF Cream. Of these, 1220 subjects were treated once daily for up to 12 weeks and 453 were treated once daily for up to 1 year.
Adverse reactions reported in the 2 randomized, double-blind, vehicle-controlled 12-week clinical trials in ≥1.0% of subjects treated with AKLIEF Cream (and for which the rate exceeded the rate for vehicle), as well as the corresponding rates reported in subjects treated with the vehicle cream are presented in Table 1.

Table 1. Adverse Reactions Occurring in ≥ 1.0% of Subjects with Acne Vulgaris of the Face and Trunk in the Two 12-week Phase 3 Clinical Trials
Preferred Term | AKLIEF Cream (N=1220) | Vehicle Cream (N=1200)
Application site irritation | 91 (7.5) | 4 (0.3)
Application site pruritus | 29 (2.4) | 10 (0.8)
Sunburn | 32 (2.6) | 6 (0.5)

Additional adverse reactions that were reported in more than one subject treated with AKLIEF Cream (and at a frequency <1%) included application site pain, application site dryness, application site discoloration, application site rash, application site swelling, application site erosion, acne, dermatitis allergic, and erythema.
In the one-year, open-label safety trial that included 453 subjects 9 years and older, with acne vulgaris of the face and trunk, the pattern of adverse reactions for AKLIEF Cream was similar to that experienced in the 12-week controlled trials. A total of 12.6% of subjects had at least one adverse reaction during the trial, and 2.9% of subjects had an adverse reaction leading to treatment discontinuation. The most common adverse reactions (≥1% of subjects) for the entire trial were application site pruritus (4.6%), application site irritation (4.2%), and sunburn (5.5%). The frequency of adverse reactions decreased over time.
Skin irritation was evaluated by active assessment of erythema, scaling, dryness, and stinging/burning and collected separately. In the two 12-week Phase 3 clinical trials, these signs/symptoms were assessed at baseline and at least one post-baseline visit, in 1214 subjects (for face) and 1202 subjects (for trunk) treated with AKLIEF Cream. The percentage of subjects who were assessed to have these signs and symptoms at any post baseline visit and at a severity worse than baseline are summarized in Table 2.

Table 2. Application Site Tolerability Reactions at Any Post Baseline Visit
Face | AKLIEF Cream N=1214 Maximum Severity during Treatment |  |  | Vehicle Cream N=1194 Maximum Severity during Treatment
 | Mild | Moderate | Severe | Mild | Moderate | Severe
Erythema | 30.6% | 28.4% | 6.2% | 21% | 6.8% | 0.8%
Scaling | 37.5% | 27.1% | 4.9% | 23.7% | 5.9% | 0.3%
Dryness | 39% | 29.7% | 4.8% | 29.9% | 6.8% | 0.8%
Stinging/Burning | 35.6% | 20.6% | 5.9% | 15.9% | 3.8% | 0.5%
Trunk | N=1202 |  |  | N=1185
Erythema | 26.5% | 18.9% | 5.2% | 12.7% | 4.4% | 0.4%
Scaling | 29.7% | 13.7% | 1.7% | 13.2% | 2.6% | 0.1%
Dryness | 32.9% | 16.1% | 1.8% | 17.8% | 3.9% | 0.1%
Stinging/Burning | 26.1% | 10.9% | 4.3% | 9.2% | 2.2% | 0.5%

Local tolerability on the face in subjects treated with AKLIEF Cream worsened for any of the signs/symptoms compared with baseline to a score of moderate for up to 30% of subjects, or severe for up to 6% of subjects. On the trunk, the corresponding percentages were up to 19% (moderate) and up to 5% (severe). The scores reached maximum severity at Week 1 for the face, and at Week 2 to 4 of treatment for the trunk, and decreased thereafter.
In the open-label, 1-year Phase 3 trial, the local tolerability profile was comparable to that observed in the two pivotal Phase 3 trials.

7 DRUG INTERACTIONS

Topical application of AKLIEF Cream is not expected to affect the circulating concentrations of oral hormonal contraceptives containing ethinyl estradiol and levonorgestrel.

8 USE IN SPECIFIC POPULATIONS

8.1 Pregnancy

Risk Summary
Available data from clinical trials with AKLIEF Cream use in pregnant women have not identified a drug-associated risk of major birth defects, miscarriage or adverse maternal or fetal outcomes. There are case reports of major birth defects similar to those seen in fetuses exposed to oral retinoids in pregnant women exposed to other topical retinoids, but these case reports do not establish a pattern or association with retinoid-related embryopathy.
In animal reproduction studies, oral doses of trifarotene administered to pregnant rats and rabbits during organogenesis that resulted in systemic exposures more than 800 times the systemic exposure at the maximum recommended human dose (MRHD) of AKLIEF Cream resulted in adverse fetal effects, including fetal deaths and external, visceral, and skeletal malformations (see Data). The background risk of major birth defects and miscarriage for the indicated population is unknown. All pregnancies have a background risk of birth defect, loss, or other adverse outcomes. In the US general population, the estimated background risk of major birth defects and miscarriage in clinically recognized pregnancies is 2% to 4% and 15% to 20%, respectively.

Data
Animal Data
Oral administration of trifarotene to pregnant rats during the period of organogenesis at doses that resulted in systemic exposures greater than 1600 times those in humans at the MRHD of AKLIEF Cream resulted in adverse fetal effects, including fetal deaths, reduced mean fetal weight, and external, visceral, and skeletal malformations.
Oral administration of trifarotene to pregnant rabbits during the period of organogenesis at doses that resulted in systemic exposures at least 800 times those in humans at the MRHD of AKLIEF Cream resulted in adverse fetal effects, including defects of the tail, limbs, urogenital organs, and vertebral column.
Trifarotene administered orally to female rats from gestation Day 6 to lactation Day 20, at doses that resulted in systemic exposures up to 594 times those in humans at the MRHD of AKLIEF Cream, had no effect on maternal function or behavior, including gestation, delivery, pup-rearing, lactation and nursing, or survival or development of pups .There were no effects of maternal treatment on behavior, learning, memory, or reproductive function of pups.

8.2 Lactation

Risk Summary
There are no data on the presence of trifarotene in human milk, the effects on the breastfed infant, or the effects on milk production. In animal studies, trifarotene was present in rat milk with oral administration of the drug. When a drug is present in animal milk, it is likely that the drug will be present in human milk. It is possible that topical administration of large amounts of trifarotene could result in sufficient systemic absorption to produce detectable quantities in human milk (see Clinical Considerations). The developmental and health benefits of breastfeeding should be considered along with the mother’s clinical need for AKLIEF Cream and any potential adverse effects on the breastfed infant from AKLIEF Cream or from the underlying maternal condition.
Clinical Considerations
To minimize potential exposure to the breastfed infant via breastmilk, use AKLIEF Cream on the smallest area of skin and for the shortest duration possible while breastfeeding. Advise breastfeeding women not to apply AKLIEF Cream directly to the nipple and areola to avoid direct infant exposure.

8.4 Pediatric Use

Safety and effectiveness of AKLIEF Cream for the topical treatment of acne vulgaris have been established in pediatric patients age 9 years to 17 years based on evidence from well-controlled clinical trials, a long-term safety trial, and a pharmacokinetic trial. A total of 897 pediatric subjects aged 9 to 17 years received AKLIEF Cream in the clinical trials [see Clinical Pharmacology (12.3) and Clinical Studies (14)] .
Safety and effectiveness of AKLIEF Cream have not been established in pediatric subjects under the age of 9 years.

8.5 Geriatric Use

Clinical trials of AKLIEF Cream did not include any subjects aged 65 years and over to determine whether they respond differently than younger subjects.

11 DESCRIPTION

AKLIEF Cream for topical administration contains 0.005% (50 mcg/g) trifarotene. Trifarotene is a terphenyl acid derivative and is a retinoid. The chemical name of trifarotene is 3”-tert-Butyl-4’-(2-hydroxy-ethoxy)-4”-pyrrolidin-1-yl-[1,1’,3’,1”]terphenyl-4- carboxylic acid. Trifarotene has the molecular formula of C29H33NO4, the molecular weight of 459.58, and the following structural formula:

Trifarotene is a white to off-white to slightly yellow powder with the melting point of 245°C. It is practically insoluble in water with pKa1 of 5.69 and pKa2 of 4.55.
AKLIEF (trifarotene) Cream 0.005% contains the following inactive ingredients: allantoin, copolymer of acrylamide and sodium acryloyldimethyltaurate dispersion 40% in isohexadecane, cyclomethicone, 95% (v/v) ethanol, medium-chain triglycerides, phenoxyethanol, propylene glycol, purified water.

12 CLINICAL PHARMACOLOGY

12.1 Mechanism of Action

Trifarotene is an agonist of retinoic acid receptors (RAR), with particular activity at the gamma subtype of RAR. Stimulation of RAR results in modulation of target genes which are associated with various processes, including cell differentiation and mediation of inflammation. The exact process by which trifarotene ameliorates acne is unknown.

12.2 Pharmacodynamics

At the approved recommended dosage, AKLIEF Cream does not prolong the QT interval to any clinically relevant extent.

12.3 Pharmacokinetics

Pharmacokinetics of trifarotene was evaluated in a study involving 19 adult subjects with acne vulgaris following once daily application of AKLIEF Cream for 29 days (daily dose range 1.5 g/day to 2 g/day) to the face, shoulders, chest and upper back.
Absorption:
Systemic concentrations were at steady state following 2 weeks of treatment and were quantifiable in 7 subjects. Steady state Cmaxranged from below the limit of quantification (less than 5 pg/mL) to 10 pg/mL and AUC0-24hranged from 75 to 104 pg.h/mL in adults. No drug accumulation is expected with long-term use.

Distribution
Plasma protein binding is approximately 99.9%

Elimination
The terminal half-life ranged from 2 to 9 hours.
Metabolism
Trifarotene is primarily metabolized by CYP2C9, CYP3A4, CYP2C8, and to a lesser extent by CYP2B6 in vitro.
Excretion
Trifarotene is primarily excreted by the feces.

Specific Populations
Pediatric Patients
Steady state Cmaxranged from less than 5 pg/mL to 9 pg/mL and AUC0-24hranged from 89 to 106 pg.h/mL in pediatrics (10 to 17- years-old). Steady state conditions were achieved in patients following 2 weeks of topical administration. No drug accumulation is expected with long-term use.

Drug Interactions Studies
Clinical Studies and Model-Based Approaches
No clinically significant differences in the pharmacokinetics of trifarotene were predicted when used concomitantly with fluconazole (a moderate CYP2C9 and CYP3A inhibitor).

In Vitro Studies
Cytochrome P450 (CYP) Enzymes: AKLIEF Cream is not expected to inhibit CYP1A2, 2B6, 2C8, 2C9, 2C19, 2D6 and 3A4, or induce CYP1A2, 2B6, and 3A4.
Transporter Systems: AKLIEF Cream is not expected to inhibit MATE, OATP, OAT, OCT, BCRP, P-gp, BSEP, or MRP.

13. NONCLINICAL TOXICOLOGY

13.1 Carcinogenesis, Mutagenesis, Impairment of Fertility

Trifarotene was not carcinogenic when topically applied to mice daily for up to 24 months in the vehicle of the product (AKLIEF Cream) at concentrations of 0.0005% or 0.001% w/w. The systemic exposures at the highest doses evaluated in mice were approximately 82 (males) and 99 (females) times higher than the human exposure at the MRHD of AKLIEF Cream.
Trifarotene was not carcinogenic when administered orally to rats daily for up to 24 months at doses up to 0.75 mg/kg/day in males and 0.2 mg/kg/day in females. The systemic exposures at the highest doses evaluated in rats were approximately 645 (males) and 1642 (females) times higher than the human exposure at the MRHD of AKLIEF Cream.

Trifarotene was negative in an in vitro bacterial reverse mutation (Ames) assay, an in vitro micronucleus assay in primary human lymphocytes, an in vitro mouse lymphoma assay with L5178Y/TK+/-cells, and an in vivo micronucleus assay in rats.
Trifarotene was assessed for effects on fertility or general reproductive function in rats. Males received trifarotene via oral gavage for 4 weeks prior to mating, during mating, and up to scheduled termination (approximately 6 weeks in total), and females were treated via oral gavage for 2 weeks prior to mating through Day 7 of gestation. No adverse effects on fertility or reproductive parameters, including sperm motility and concentration, were observed at the highest doses evaluated, which resulted in systemic exposures approximately 1755 (males) and 1726 (females) times higher than the human exposure at the MRHD of AKLIEF Cream.

14 CLINICAL STUDIES

AKLIEF Cream applied once daily in the evening was evaluated in the treatment of moderate facial and truncal acne vulgaris in two randomized, multicenter, parallel group, double-blind, vehicle-controlled trials of identical design, Study 1 (NCT02566369) and Study 2 (NCT02556788). The trials were conducted in a total of 2420 subjects aged 9 years and older, who were treated for up to 12 weeks with either AKLIEF Cream (1214 subjects) or vehicle cream (1206 subjects). Subjects were encouraged to use a moisturizer as desired, while allowing an interval of approximately 1 hour before or after the study treatment application.
Acne severity was evaluated using a 5-point Investigator’s Global Assessment (IGA) scale for the face and a 5-point Physician’s Global Assessment (PGA) scale for the trunk with moderate acne vulgaris defined as a score of 3. Overall, 87% of subjects were Caucasian and 55% were female. Thirty-four (1.4%) subjects were 9 to 11 years of age, 1128 (47%) subjects were 12 to 17 years of age, and 1258 (52%) subjects were 18 years and older. All subjects had moderate acne vulgaris on the face and 99% of subjects had moderate acne vulgaris on the trunk. At baseline, subjects had between 7 and 200 (average 36) inflammatory lesions on the face and between 0 and 220 (average 38) on the trunk. Additionally, subjects had 21 to 305 (average 52) non-inflammatory lesions on the face and 0 to 260 (average 46) on the trunk.
Success on the IGA/PGA scale was defined as achieving a score of 0 (clear) or 1 (almost clear) and at least a 2-grade improvement from baseline. The co-primary endpoints (evaluated on the face) were the percentage of subjects achieving success on the IGA scale, the mean absolute change in facial inflammatory lesion count from baseline, and the mean absolute change in facial non-inflammatory lesion count from baseline, all evaluated at Week 12. The co-secondary endpoints (evaluated on the trunk) were the percentage of subjects achieving success on the PGA scale, the mean absolute change in truncal inflammatory lesion count from baseline, and the mean absolute change in truncal non-inflammatory lesion count from baseline, all evaluated at Week 12. Efficacy results for acne on the face and trunk after 12 weeks of treatment are presented in Tables 3 and 4 respectively.

Table 3. Acne of the Face Efficacy Results at Week 12 (Intent-to-Treat; Multiple Imputation)
 | Study 1 |  | Study 2
 | AKLIEF Cream | Vehicle Cream | AKLIEF Cream | Vehicle Cream
 | (N=612) | (N=596) | (N=602) | (N=610)
IGA Success At least a 2-grade improvement and "Clear" (0) or "Almost Clear" (1) | 29.4% | 19.5% | 42.3% | 25.7%
Inflammatory Lesions Mean [Means presented in table are Least Square (LS) means] Absolute (Percent) Change from Baseline | -19.0 (-54.4%) | -15.4 (-44.8%) | -24.2 (-66.2%) | -18.7 (-51.2%)
Non-inflammatory Lesions Mean Absolute (Percent) Change from Baseline | -25.0 (-49.7%) | -17.9 (-35.7%) | -30.1 (-57.7%) | -21.6 (-43.9%)

Table 4. Acne of the Trunk Efficacy Results at Week 12 (Intent-to-Teat on the Trunk; Multiple Imputation)
 | Study 1 |  | Study 2
 | AKLIEF Cream | Vehicle Cream | AKLIEF Cream | Vehicle Cream
 | (N=600) | (N=585) | (N=598) | (N=609)
PGA Success At least a 2-grade improvement and "Clear" (0) or "Almost Clear" (1) | 35.7% | 25.0% | 42.6% | 29.9%
Inflammatory Lesions Mean [Means presented in table are Least Square (LS) means] Absolute (Percent) Change from Baseline | -21.4 (-57.4%) | -18.8 (-50.0%) | -25.5 (-65.4%) | -19.8 (-51.1%)
Non-inflammatory Lesions Mean Absolute (Percent) Change from Baseline | -21.9 (-49.1%) | -17.8 (-40.3%) | -25.9 (-55.2%) | -20.8 (-45.1%)

16 HOW SUPPLIED/STORAGE AND HANDLING

AKLIEF Cream, 0.005% is provided as a white cream supplied in the following packaging configurations with corresponding NDC numbers:

- 45-gram pump NDC 0299-5935-45

Storage and Handling
- Store at 20˚ to 25˚C (68˚ to 77˚F); excursions permitted to 15° to 30°C (59° to 86°F)..
- Keep away from heat.
- Keep out of reach of children.

17 PATIENT COUNSELING INFORMATION

See FDA-approved patient labeling (Patient Information).

Advise the patient to:

- Cleanse the area to be treated; pat dry. Apply AKLIEF Cream as a thin layer once daily in the evening to the face, avoiding the eyes, lips, nasolabial folds, and mucous membranes. A thin layer of AKLIEF Cream may also be applied to the chest, shoulders, and back.
- Avoid applying AKLIEF Cream to damaged skin (such as cuts, abrasions), eczematous areas, and sunburned skin.
- Reduce the risk of such irritation, use a moisturizer from the start of treatment, and, if appropriate, reduce the frequency of application of AKLIEF Cream or suspend use temporarily. AKLIEF Cream may cause irritation such as erythema, scaling, dryness, and stinging or burning.
- Minimize exposure to sunlight, including sunlamps and phototherapy devices.
- Use sunscreen products and protective apparel (e.g., hat) over treated areas when exposure to sunlight cannot be avoided.
- Avoid concomitant use of other potentially irritating topical products (medicated or not).
- Use AKLIEF Cream on the smallest area of skin and for the shortest duration possible while breastfeeding. Advise breastfeeding women not to apply AKLIEF Cream directly to the nipple and areola to avoid direct infant exposure.

Marketed by:
GALDERMA LABORATORIES, L.P.
Dallas, Texas 75201 USA
Made in Canada
All trademarks are the property of their respective owners.

Patient Information
AKLIEF® (trifarotene) cream

Important:AKLIEF Cream is for use on the skin only. Do not use AKLIEF Cream in your mouth eyes, or vagina.

What is AKLIEF Cream?
AKLIEF Cream is a prescription medicine used on the skin (topical) to treat acne vulgaris in people 9 years of age and older.
It is not known if AKLIEF Cream is safe and effective in children younger than 9 years old.

Before using AKLIEF Cream, tell your healthcare provider about all of your medical conditions, including if you :

- have skin problems, including eczema, cuts or sunburn
- are pregnant or planning to become pregnant. It is not known if AKLIEF Cream can harm your unborn baby.
- are breastfeeding or plan to breastfeed. It is not known if AKLIEF Cream passes into your breast milk. Breastfeeding women should use AKLIEF Cream on the smallest area of skin and for the shortest time needed while breastfeeding.
  Do not apply AKIEF Cream to the nipple and areola to avoid contact with your baby.

Tell your healthcare provider about all the medicines you take,including prescription and over-the-couter medicines, vitamins and herbal supplements.
Especially tell your healthcare provider if you use any other medicine for acne.

How should I use AKLIEF Cream?

- Use AKLIEF Cream exactly as your healthcare provider tell you to use it. Apply a thin layer of AKLIEF Cream over the affected areas 1 time each day, in the evening.

Applying AKLIEF Cream:

- Wash the area where the cream will be applied and pat dry.
- If you receive a sample tube of AKLIEF Cream, follow your healthcare provider’s instructions about how much to apply.
- AKLIEF Cream comes in a pump.
  - Press down on (depress) the pump 1 time to dispense a small amount of AKLIEF Cream and spread a thin layer over your face (forehead, cheeks, nose, and chin). Avoid contact with your eyes, lips, mouth, and the corners of your nose.
  - Press down on the pump 2 times to dispense enough AKLIEF Cream to apply a thin layer to cover your upper trunk (the area of your upper back that you can reach, shoulders, and chest). One more pump may be used to apply a thin layer of AKLIEF Cream to your middle and lower back, if acne is present.
- When you begin treatment with AKLIEF Cream, you should begin applying a moisturizer on your skin as often as needed. See “Local skin irritation”below.

What should I avoid while using AKLIEF Cream?

- Minimize exposure to sunlight. You should avoid using sunlamps, tanning beds, and ultraviolet light during treatment with AKLIEF Cream. If you have to be in sunlight or are sensitive to sunlight, use a sunscreen with a SPF (sun protection factor) of 15 or more, and wear protective clothing and a wide-brimmed hat to cover the treated areas.
- Avoid using AKLIEF Cream on skin areas with cuts, abrasions, eczema, or on sunburned skin.
- Avoid using skin products that may dry or irritate your skin, such as:
  - medicated or abrasive soaps and cleansers
  - soaps, cleansers, and cosmetics that have strong skin drying effects
  - products that contain high amounts of alcohol
- Avoid the use of “waxing” as a hair removal method on skin treated with AKLIEF Cream.

What are the possible side effects of AKLIEF Cream?
AKLIEF Cream may cause serious side effects including:

- Local skin irritation.Local skin reactions are common with AKLIEF Cream, are most likely to happen during the first 4 weeks of treatment and may decrease with continued use of AKLIEF Cream. Signs and symptoms of local skin reactions include:
  - redness
  - scaling
  - dryness
  - stinging or burning

To help reduce your risk of developing these local skin reactions, when you begin treatment with AKLIEF Cream, you should begin applying a moisturizer on your skin as often as needed.
Tell your healthcare provider if you develop symptoms of a local skin reaction. Your doctor may tell you to use AKLIEF Cream less often, or temporarily, or permanently stop your treatment with AKLIEF Cream.

The most common side effects of AKLIEF Cream include: itching and sunburn. See “What should I avoid while using AKLIEF Cream.
These are not all the possible side effects of AKLIEF Cream. For more information, ask your healthcare provider or pharmacist.
Call your doctor for medical advice about side effects. You may report side effects to FDA at 1-800-FDA-1088.
You may also report side effects to GALDERMA LABORATORIES, L.P. at 1-866-735-4137.

How should I store AKLIEF Cream?

- Store AKLIEF Cream at 20° to 25°C (68° to 77°F); excursions permitted to 15° to 30°C (59° to 86°F)
- Keep AKLIEF Cream away from heat.
- If you receive a sample tube of AKLIEF Cream from your healthcare provider, keep the tube tightly closed.

Keep AKLIEF Cream and all medicines out of the reach of children.

General information about the safe and effective use of AKLIEF Cream.
Medicines are sometimes prescribed for purposes other than those listed in a Patient Information Leaflet. Do not use AKLIEF Cream for a condition for which it was not prescribed. Do not give AKLIEF Cream to other people, even if they have the same symptoms you have. It may harm them.
You can ask your pharmacist or healthcare provider for information about AKLIEF Cream that is written for health professionals.

What are the ingredients in AKLIEF Cream?
Active ingredient: trifarotene
Inactive ingredients:allantoin, copolymer of acrylamide and sodium acryloyldimethyltaurate dispersion 40% in isohexadecane, cyclomethicone, 95% (v/v) ethanol, medium-chain triglycerides, phenoxyethanol, propylene glycol, purified water.
Marketed by: GALDERMA LABORATORIES, L.P., Dallas, Texas 75201 USA
All trademarks are the property of their respective owners.
Made in Canada
This Patient Information has been approved by the U.S. Food and Drug Administration.
Revised: 10/2023
P54485-3

PACKAGE LABEL 45g CARTON

RX only
NDC 0299-5935-45
AKLIEF
(trifarotene)
Cream, 0.005%
PUMP
For topical use only
NET WT.
45 g
GALDERMA

For topical use only
Not for oral, ophthalmic or intravaginal use
USUAL DOSAGE:
Apply a thin layer to affected areas of the face and / or trunk once a day. See package insert for complete prescribing information.
EACH GRAM CONTAINS:
Active:trifarotene 0.005%
Inactive:allantoin, copolymer of acrylamide and sodium acryloyldimethyltaurate dispersion 40% in isohexadecane, cyclomethicone, 95% (v/v) ethanol, medium-chain triglycerides, phenoxyethanol, propylene glycol, purified water. Contains 5% alcohol
STORAGE:
Store at 20º to 25ºC (68º to 77ºF); excursions permitted between 15º and 30ºC (59º to 86ºF). See carton closure for lot number and expiration.

Marketed by:
GALDERMA LABORATORIES, L.P.
Dallas, TX 75201 USA
Made in Canada
All trademarks are the property of their respective owners.
P54484-1
NET WT. 45 g